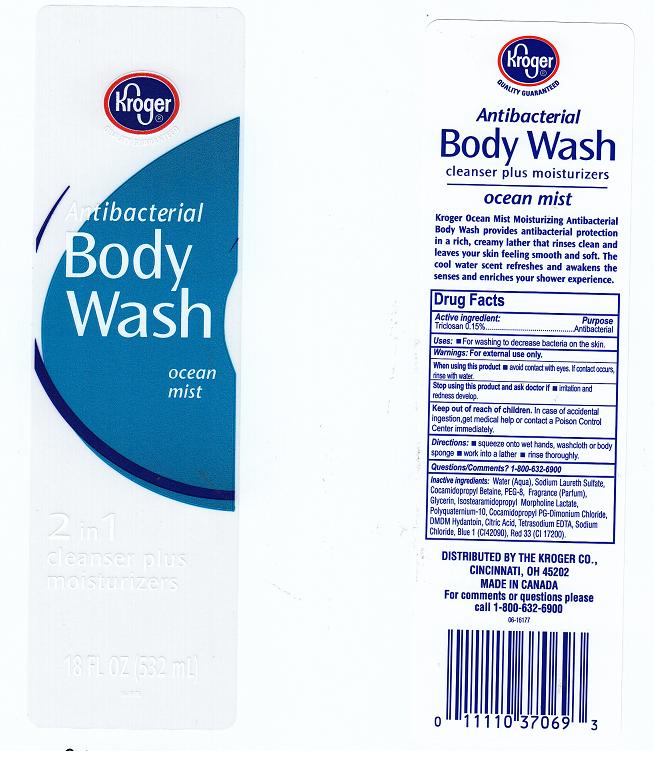 DRUG LABEL: ANTIBACTERIAL BODY WASH
NDC: 30142-801 | Form: LIQUID
Manufacturer: THE KROGER COMPANY
Category: otc | Type: HUMAN OTC DRUG LABEL
Date: 20110609

ACTIVE INGREDIENTS: TRICLOSAN 0.15 mL/100 mL
INACTIVE INGREDIENTS: WATER; SODIUM LAURETH SULFATE; COCAMIDOPROPYL BETAINE; POLYETHYLENE GLYCOL 400; GLYCERIN; MORPHOLINE; POLYQUATERNIUM-10 (400 CPS AT 2%); COCAMIDOPROPYL PG-DIMONIUM CHLORIDE PHOSPHATE; DMDM HYDANTOIN; CITRIC ACID MONOHYDRATE; EDETATE SODIUM; SODIUM CHLORIDE; FD&C BLUE NO. 1; D&C RED NO. 33

DRUG FACTS

ACTIVE INGREDIENT

TRICLOSAN 0.15%

PURPOSE

ANTIBACTERIAL

USES

FOR WASHING TO DECREASE BACTERIA ON THE SKIN.

WARNINGS

FOR EXTERNAL USE ONLY.

WHEN USING THIS PRODUCT

AVOID CONTACT WITH EYES. IF CONTACT OCCURS, RINSE WITH WATER.

STOP USING THIS PRODUCT AND ASK DOCTOR IF

IRRITATION AND REDNESS DEVELOP.

KEEP OUT OF REACH OF CHILDREN

IN CASE OF ACCIDENTAL INGESTION, GET MEDICAL HELP OR CONTACT A POISON CONTROL CENTER IMMEDIATELY.

DIRECTIONS

SQUEEZE ONTO WET HANDS, WASHCLOTH OR BODY SPONGE. WORK INTO A LATHER. RINSE THOROUGHLY.

QUESTIONS OR COMMENTS

1-800-632-6900

INACTIVE INGREDIENTS

WATER, SODIUM LAURETH SULFATE, COCAMIDOPROPYL BETAINE, PEG-8, FRAGRANCE, GLYCERIN, ISOSTEARAMIDOPROPYL MORPHOLINE LACTATE, POLYQUATERNIUM-10, COCAMIDOPROPYL PG-DIMONIUM CHLORIDE, DMDM HYDANTOIN, CITRIC ACID, TETRASODIUM EDTA, SODIUM CHLORIDE, BLUE 1 (CI 42090), RED 33 (CI 17200).